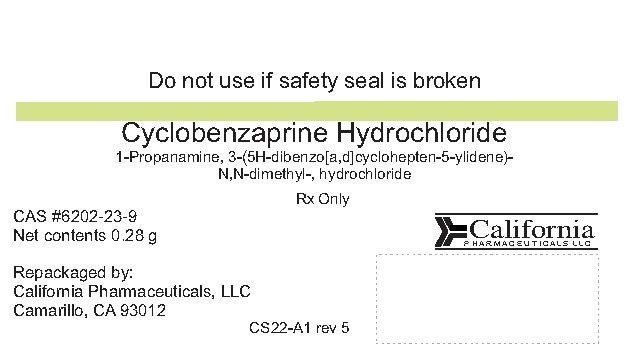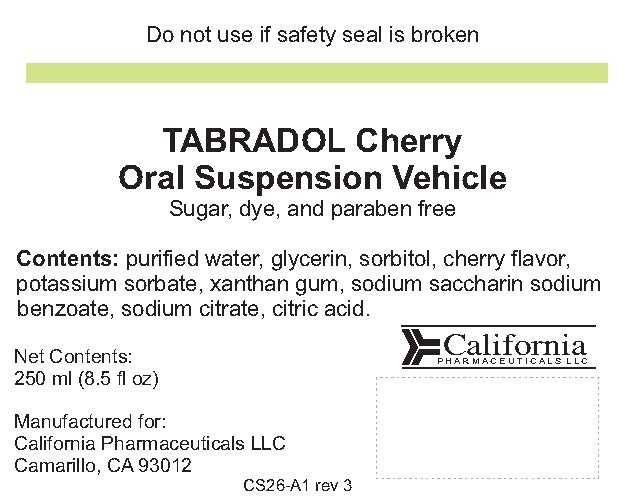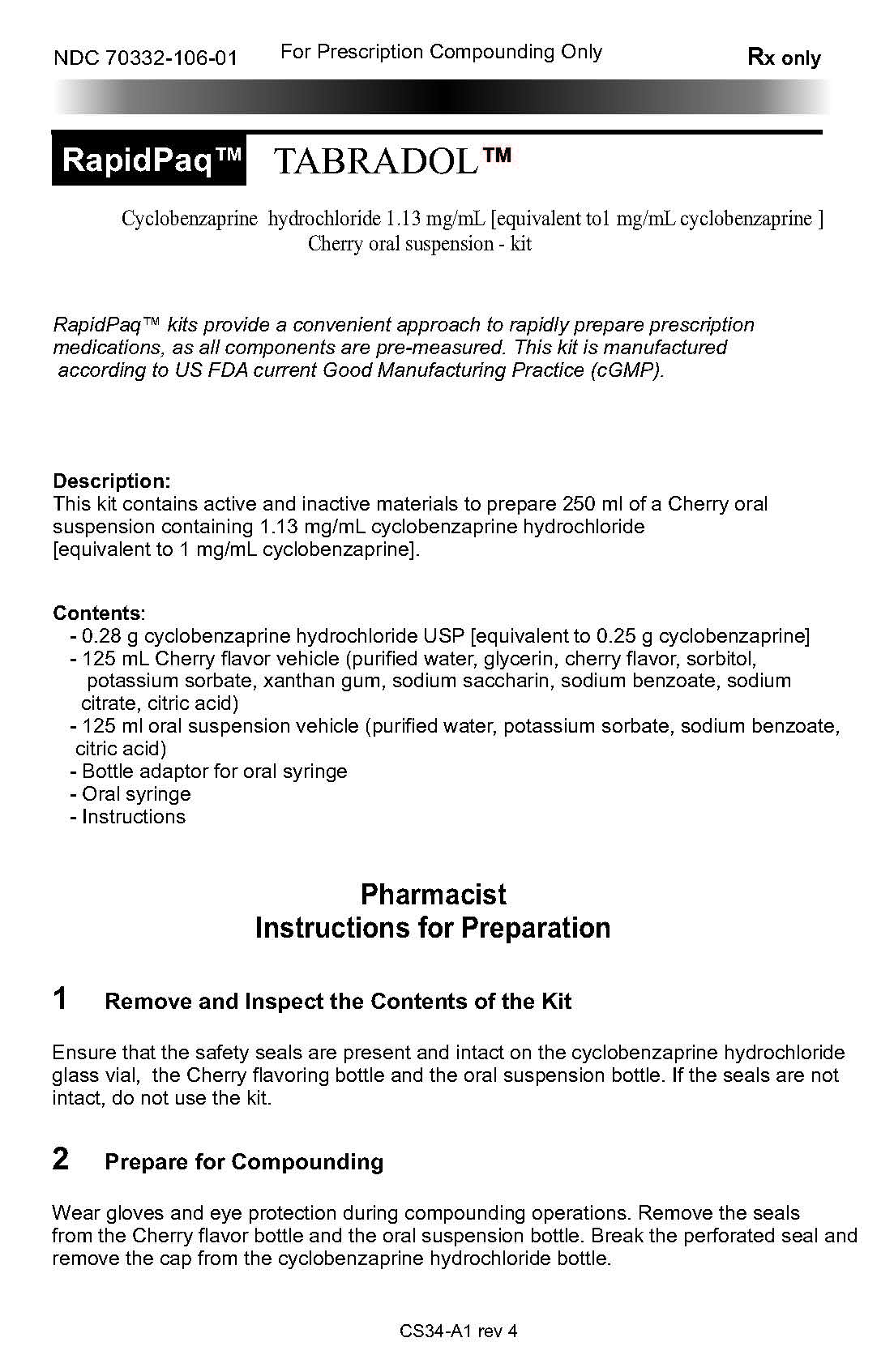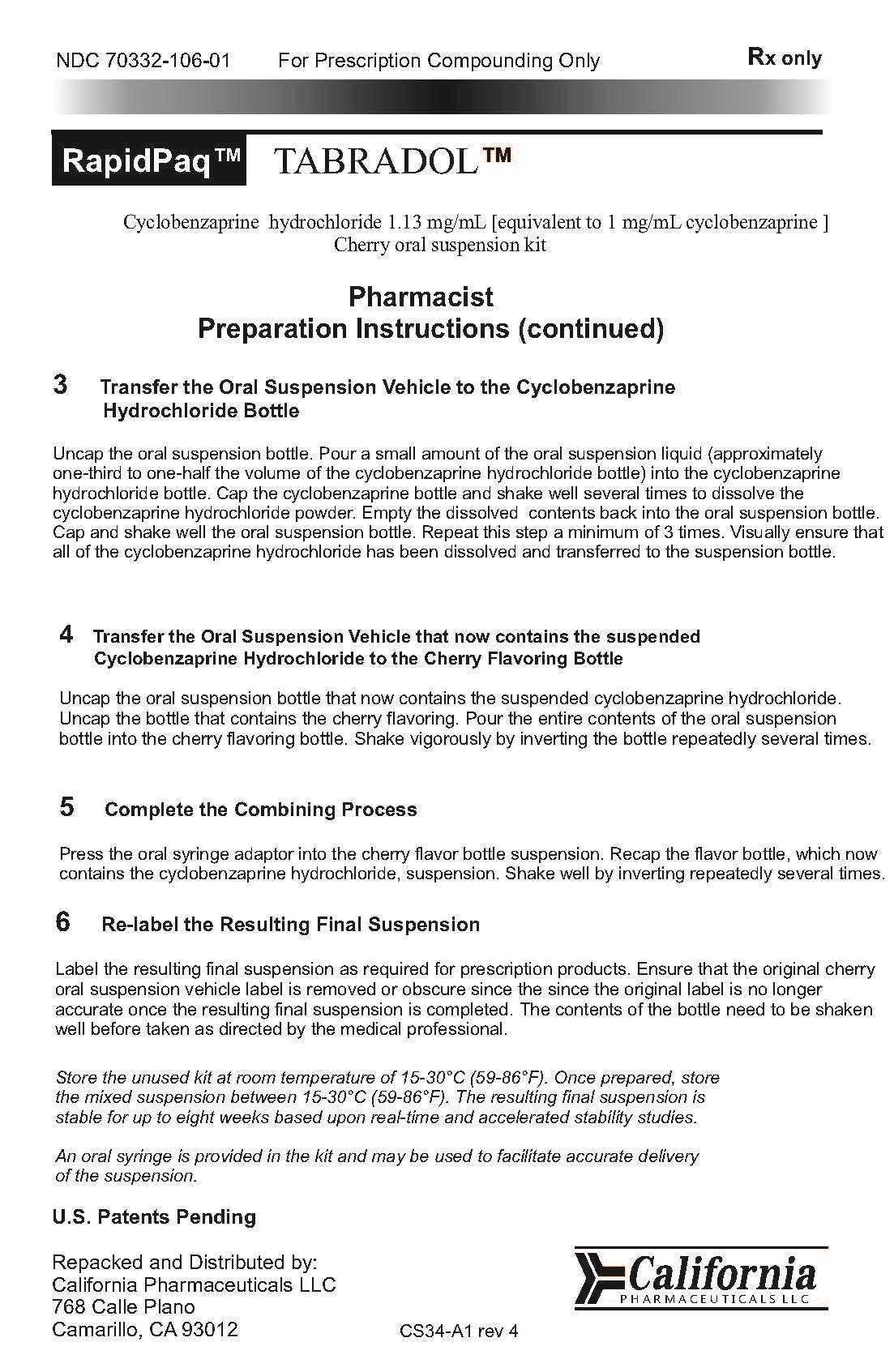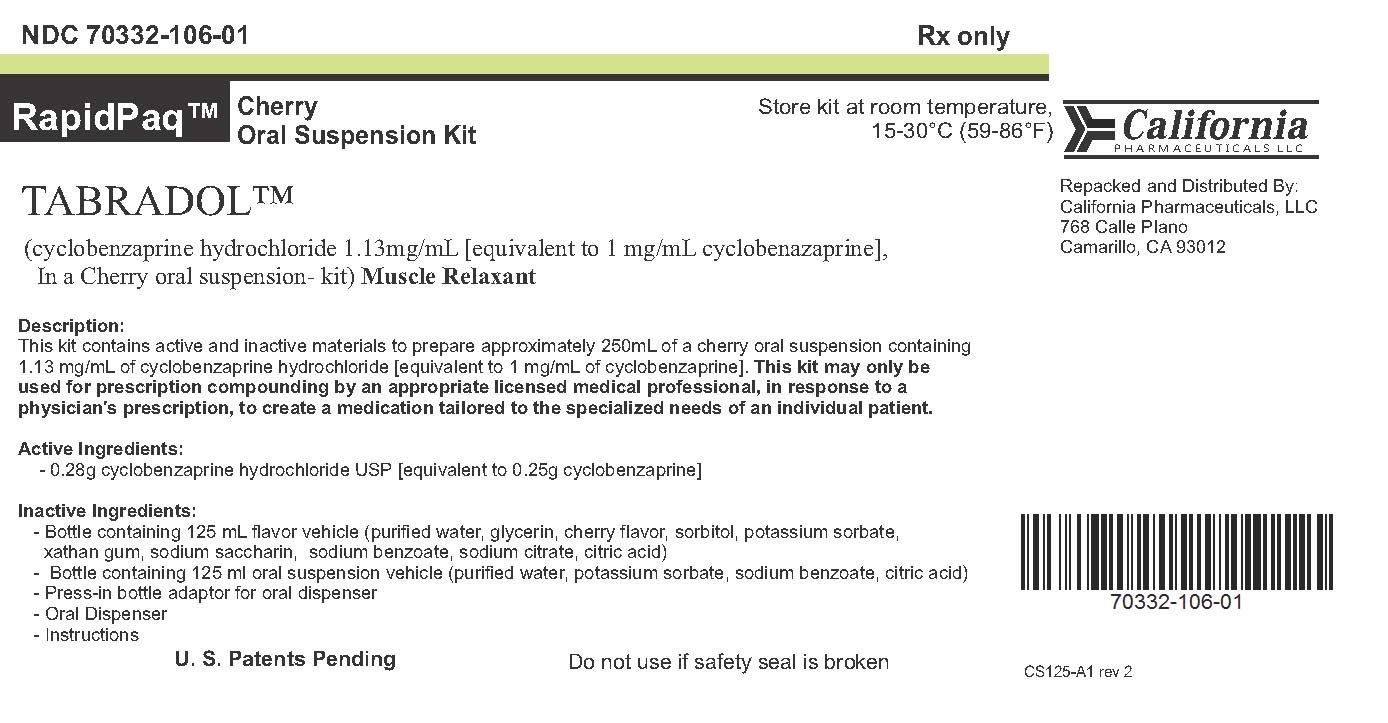 DRUG LABEL: Tabradol
NDC: 70332-106 | Form: KIT | Route: ORAL
Manufacturer: California Pharmaceuticals, LLC
Category: prescription | Type: HUMAN PRESCRIPTION DRUG LABEL
Date: 20160101

ACTIVE INGREDIENTS: CYCLOBENZAPRINE HYDROCHLORIDE 0.25 g/0.25 g
INACTIVE INGREDIENTS: SORBITOL; WATER; GLYCERIN; CITRIC ACID MONOHYDRATE; POTASSIUM SORBATE; SODIUM BENZOATE; DIMETHYL SULFONE; SACCHARIN SODIUM; GLYCERIN; CHERRY; CITRIC ACID MONOHYDRATE; SODIUM CITRATE; SODIUM BENZOATE; WATER; POTASSIUM SORBATE; XANTHAN GUM

Tabradol